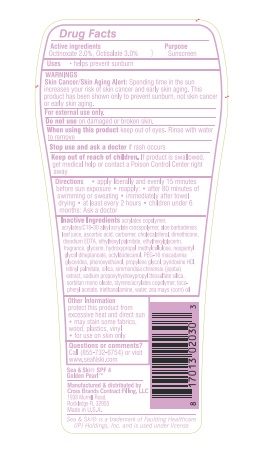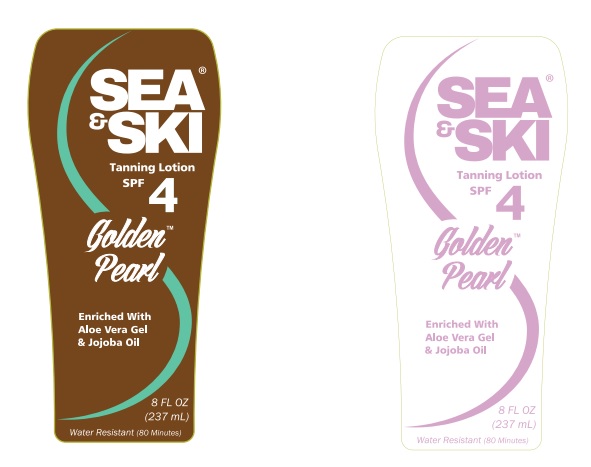 DRUG LABEL: Sea and Ski Tanning LotionSPF 4
NDC: 73440-2030 | Form: LOTION
Manufacturer: Cross Brands Contract Filling
Category: otc | Type: HUMAN OTC DRUG LABEL
Date: 20210326

ACTIVE INGREDIENTS: OCTISALATE 7.11 g/237 g; OCTINOXATE 4.74 g/237 g
INACTIVE INGREDIENTS: WATER 184.62 g/237 g

Sea & Ski Tanning Lotion SPF 4